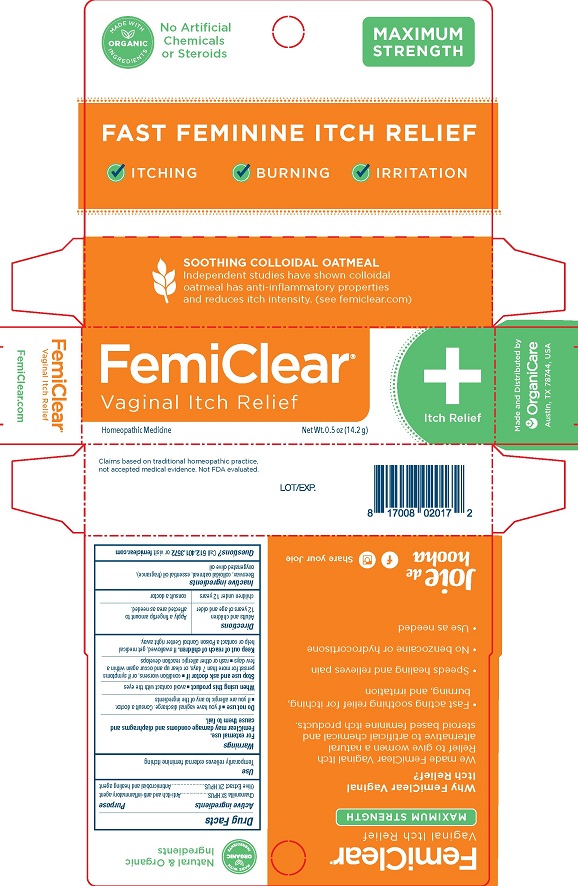 DRUG LABEL: FemiClear

NDC: 71042-010 | Form: OINTMENT
Manufacturer: Organicare Nature's Science, LLC
Category: homeopathic | Type: HUMAN OTC DRUG LABEL
Date: 20251020

ACTIVE INGREDIENTS: CHAMOMILE 3 [hp_X]/14 g; OLEA EUROPAEA FRUIT VOLATILE OIL 2 [hp_X]/14 g
INACTIVE INGREDIENTS: OATMEAL; OLIVE OIL; YELLOW WAX

FemiClear Vaginal Itch Relief

Drug Facts

Active ingredients

Chamomilla 3X HPUS

Olive Extract 2X HPUS

Purpose

Anti-itch and anti-inflammatory agent

Antimicrobial and healing agent

Use

Temporarily relieves external feminine itching

Warnings

For external use.

FemiClear may damage condoms and diaphragms and cause them to fail.

Do not use

- if you have a vaginal discharge. Consult a doctor.
- if you are allergic to any of the ingredients

When using this product

- avoid contact with the eyes

Stop use and ask a doctor if

- condition worsens, or if symptoms persist for more than 7 days, or clear up and occur again within a few days
- rash or other allergic reaction develops

Keep out of reach of children. If swallowed, get medical help or contact a Poison Control Center right away.

Directions

Adults and children 12 years of age and older | Apply a fingertip amount to affected area as needed.
children under 12 years | consult a doctor

Inactive ingredients

Beeswax, colloidal oatmeal, essential oil (fragrance), oxygenated olive oil

QUESTIONS

Questions? Call 512.401.3572 or visit femiclear.com

Claims based on traditional homeopathic practice, not accepted medical evidence. Not FDA evaluated.

Made and Distributed by

Organicare

Austin, TX 78744, USA

PACKAGE LABEL

MADE WITH ORGANIC INGREDIENTS

No Artificial Chemicals or Steroids

MAXIMUM STRENGTH

FAST FEMININE ITCH RELIEF

♦ ITCHING ♦ BURNING ♦ IRRITATION

FemiClear®

Vaginal Itch Relief

Homeopathic Medicine

Net Wt. 0.5 oz (14.2 g)